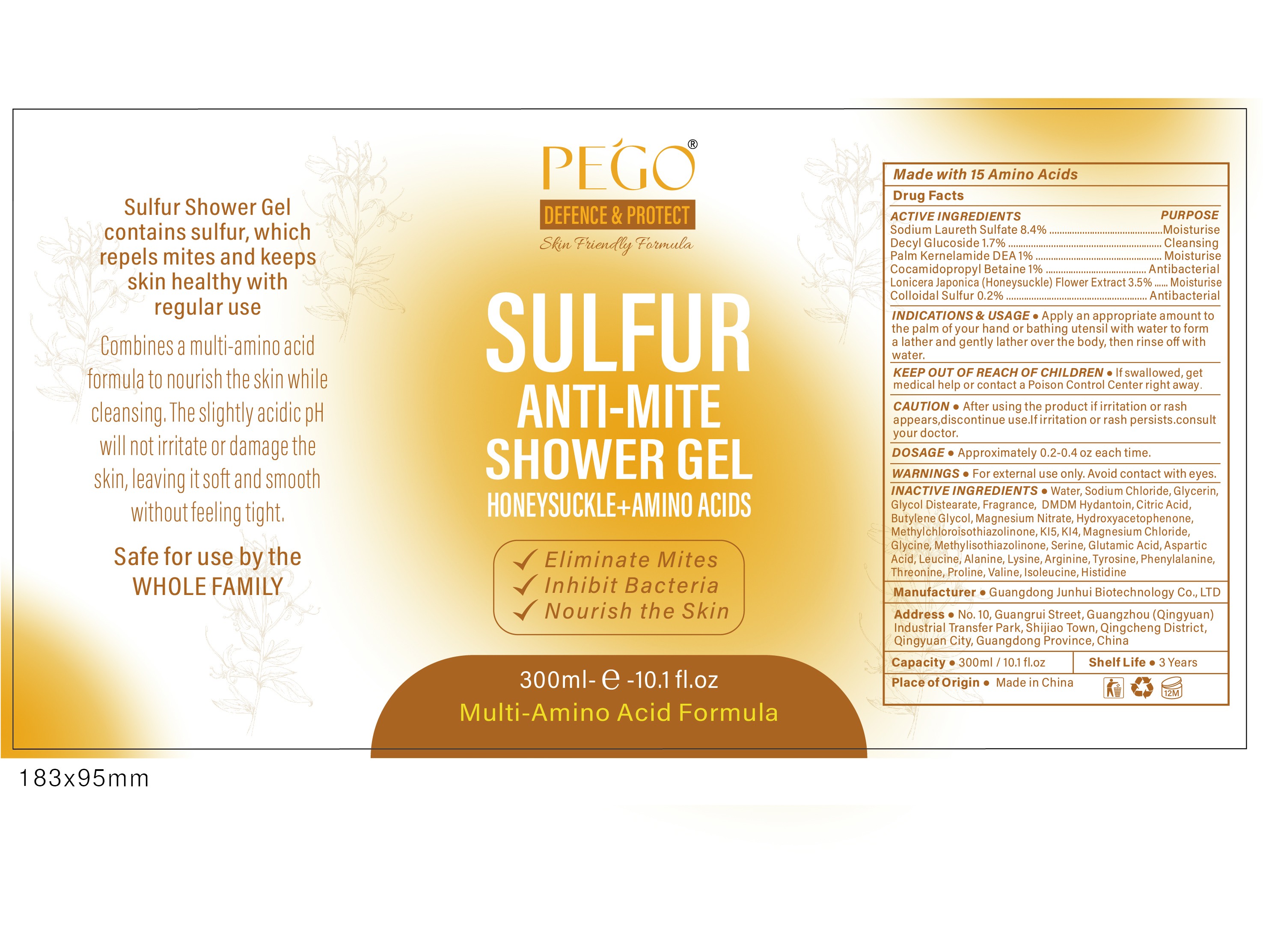 DRUG LABEL: Sulfur anti-mite shower gel
NDC: 84509-034 | Form: LIQUID
Manufacturer: Guangdong Junhui Biotechnology Co., Ltd
Category: otc | Type: HUMAN OTC DRUG LABEL
Date: 20250108

ACTIVE INGREDIENTS: SODIUM 25200 mg/300 mL; LONICERA JAPONICA FLOWER 10500 mg/300 mL; DECYL GLUCOSIDE 5100 mg/300 mL; COCAMIDOPROPYL BETAINE 3000 mg/300 mL; PALM KERNEL OIL 3000 mg/300 mL; SULFUR 600 mg/300 mL
INACTIVE INGREDIENTS: METHYLISOTHIAZOLINONE; LEUCINE; MAGNESIUM CHLORIDE; DMDM HYDANTOIN; SODIUM CHLORIDE; GLYCOL DISTEARATE; ISOLEUCINE; PROLINE; MAGNESIUM NITRATE; HISTIDINE; SERINE; GLYCINE; GLUTAMIC ACID; LYSINE; PHENYLALANINE; FRAGRANCE 13576; HYDROXYACETOPHENONE; KI5; WATER; ACONITIC ACID; KI4; BUTYLENE GLYCOL; ALANINE; THREONINE; GLYCERIN; VALINE; METHYLCHLOROISOTHIAZOLINONE; ASPARTIC ACID; TYROSINE; ARGININE

Active Ingredients

Sodium Laureth Sulfate 8.4%
Decyl Glucoside 1.7%
Palm Kernelamide DEA 1%
Cocamidopropyl Betaine 1%
Lonicera Japonica(Honeysuckle) Flower Extract 3.5%
Colloidal Sulfur 0.2%

Purpose

Moisturise
Cleansing
Antibacterial

Uses

Apply an appropriate amount to the palm of your hand or bathing utensil with water to form a lather and gently lather over the body, then rinse off with water.

Warnings

For external use only.Avoid contact with eyes.

Keep out of reach of children

If swallowed, get medical help or contact a Poison Control Center right away

CAUTION

After using the product if irritation or rash appears,discontinue use.If irritation or
rash persists.consult your doctor.

Product Name

Sulfur anti-mite shower gel

DOSAGE

Approximately 0.2-0.4 oz each time.

Inactive Ingredients

Water,Sodium Chloride,Glycerin,Glycol Distearate, Fragrance, DMDM Hydantoin, Citric Acid,Butylene Glycol,Magnesium Nitrate, Hydroxyacetophenone.Methylchloroisothiazolinone, Kl5, Kl4, Magnesium Chloride,Glycine, Methylisothiazolinone,Serine, Glutamic Acid, Aspartic Acid, Leucine,Alanine,Lysine,Arginine,Tyrosine,Phenylalanine.Threonine, Proline, Valine,lsoleucine, Histidine

Manufacturer

Guangdong Junhui Biotechnology Co.,LTD

Address

No.10,Guangrui Street,Guangzhou(Qingyuan) Industrial Transfer Park,Shijiao Town,Qingcheng District,
Qingyuan City,Guangdong Province,China

Capacity

300ml-e-10.1f1.oz

Shelf Life

3 Years

Place of Origin

Made in China